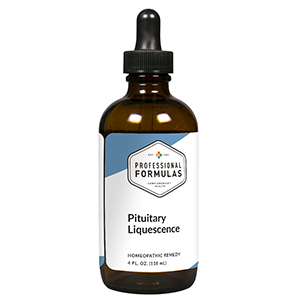 DRUG LABEL: Pituitary Liquescence
NDC: 63083-3018 | Form: LIQUID
Manufacturer: Professional Complementary Health Formulas
Category: homeopathic | Type: HUMAN OTC DRUG LABEL
Date: 20190815

ACTIVE INGREDIENTS: CORTICOTROPIN 6 [hp_X]/118 mL; CAULOPHYLLUM THALICTROIDES ROOT 6 [hp_X]/118 mL; BOS TAURUS HYPOTHALAMUS 6 [hp_X]/118 mL; SUS SCROFA PINEAL GLAND 6 [hp_X]/118 mL; BOS TAURUS PITUITARY GLAND, POSTERIOR 6 [hp_X]/118 mL; BLACK COHOSH 6 [hp_X]/118 mL; CAUSTICUM 12 [hp_X]/118 mL; SODIUM CHLORIDE 12 [hp_X]/118 mL; CINCHONA OFFICINALIS BARK 30 [hp_X]/118 mL
INACTIVE INGREDIENTS: ALCOHOL; WATER

T18

ACTIVE INGREDIENTS

Adrenocorticotrophin (ACTH) 6X
Caulophyllum thalictroides 6X
Hypothalamus 6X
Pineal 6X
Pituitary 6X
Cimicifuga racemosa 6X, 30X
Causticum 12X
Natrum muriaticum 12X
Cinchona officinalis 30X

QUESTIONS

Professional Formulas

PO Box 2034 Lake Oswego, OR 97035

INDICATIONS

For the temporary relief of poor appetite, nausea or vomiting, weakness or fatigue, dizziness, body aches, decreased libido, irregular menses, hot flashes, mood changes or swings, dry skin, constipation, memory loss, sleep disturbance, or occasional headaches.*

PURPOSE

*Claims based on traditional homeopathic practice, not accepted medical evidence. Not FDA evaluated.

WARNINGS

In case of overdose, get medical help or contact a poison control center right away.

Keep out of the reach of children.

PREGNANCY OR BREAST FEEDING

If pregnant or breastfeeding, ask a healthcare professional before use.

DIRECTIONS

Place drops under tongue 30 minutes before/after meals. Adults and children 12 years and over: Take one full dropper up to 2 times per day. Consult a physician for use in children under 12 years of age.

OTHER INFORMATION

Tamper resistant. If seal is broken, do not use. After opening, close container tightly and store at room temperature away from heat.

INACTIVE INGREDIENTS

20% ethanol, purified water.

LABEL

Est 1985

Professional Formulas

Complementary Health

Pituitary Liquescence

Homeopathic Remedy

4 FL. OZ. (118 mL)